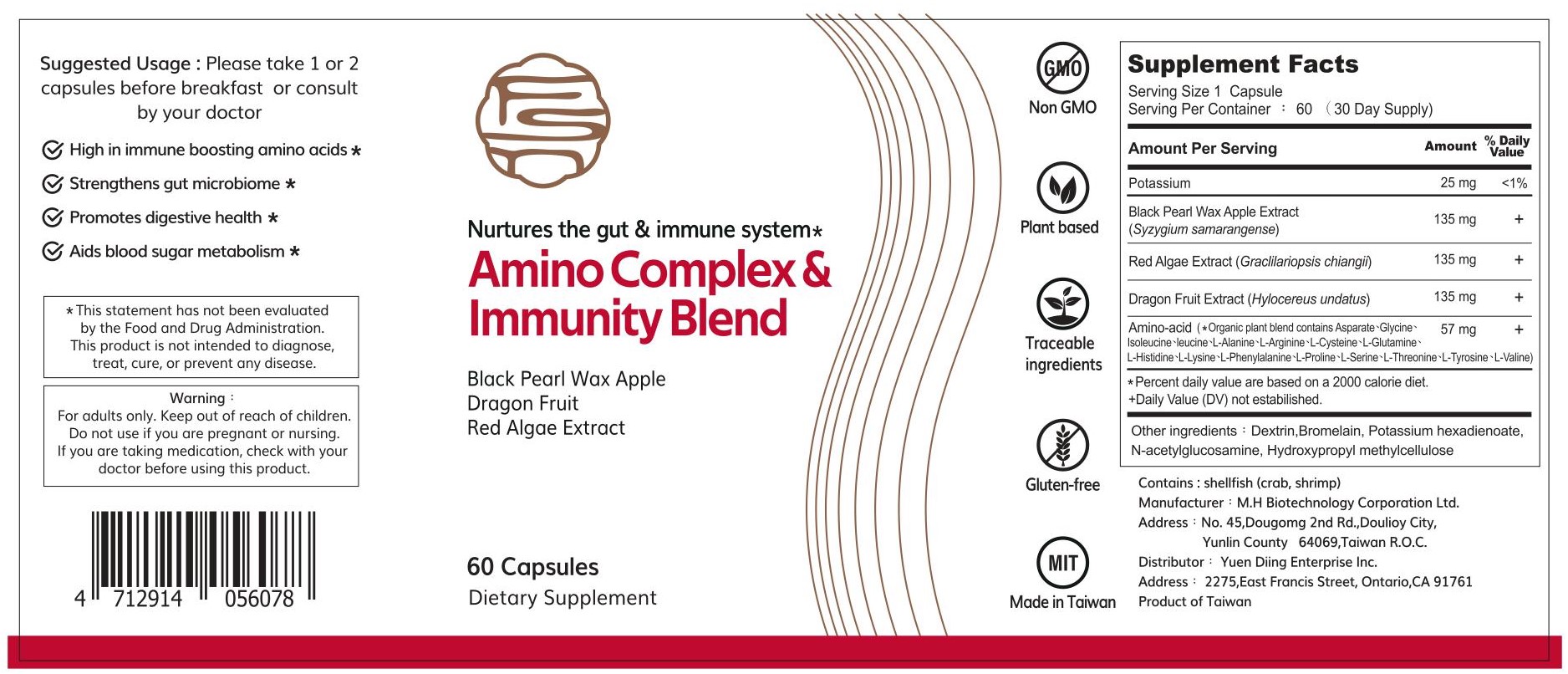 DRUG LABEL: FSN Amino Complex and Immunity Blend
NDC: 4712914056078 | Form: CAPSULE
Manufacturer: Yuen Diing Enterprise Inc.
Category: other | Type: DIETARY SUPPLEMENT
Date: 20201111

ACTIVE INGREDIENTS: SYZYGIUM JAMBOS FRUIT RIND 135 mg/410 1; HYLOCEREUS UNDATUS FRUIT 135 mg/410 1; GRACILARIA GRACILIS 135 mg/410 1; N-ACETYLGLUCOSAMINE 2 mg/410 1

HEALTH CLAIM

Nurtures the gut and immine system*

High in immune boosting amino acids*
Strengthens gut microbiome*
Promotes digestive health*
Aids blood sugar metabolism*

DOSAGE AND ADMINISTRATION

Suggested Usage：Please take 1 or 2 capsules before breakfast or consult by your doctor

WARNINGS

Warning：For adults only. Keep out of reach of children.Do not use if you are pregnant or nursing.If you are taking medication, check with your doctor before using this product.

PRECAUTIONS

*This statement has not been evaluated by the Food and Drug Administration. This product is not intended to diagnose, treat, cure, or prevent any disease.

SAFE HANDLING WARNING

Contains：shellfisf(crab, shrimp)